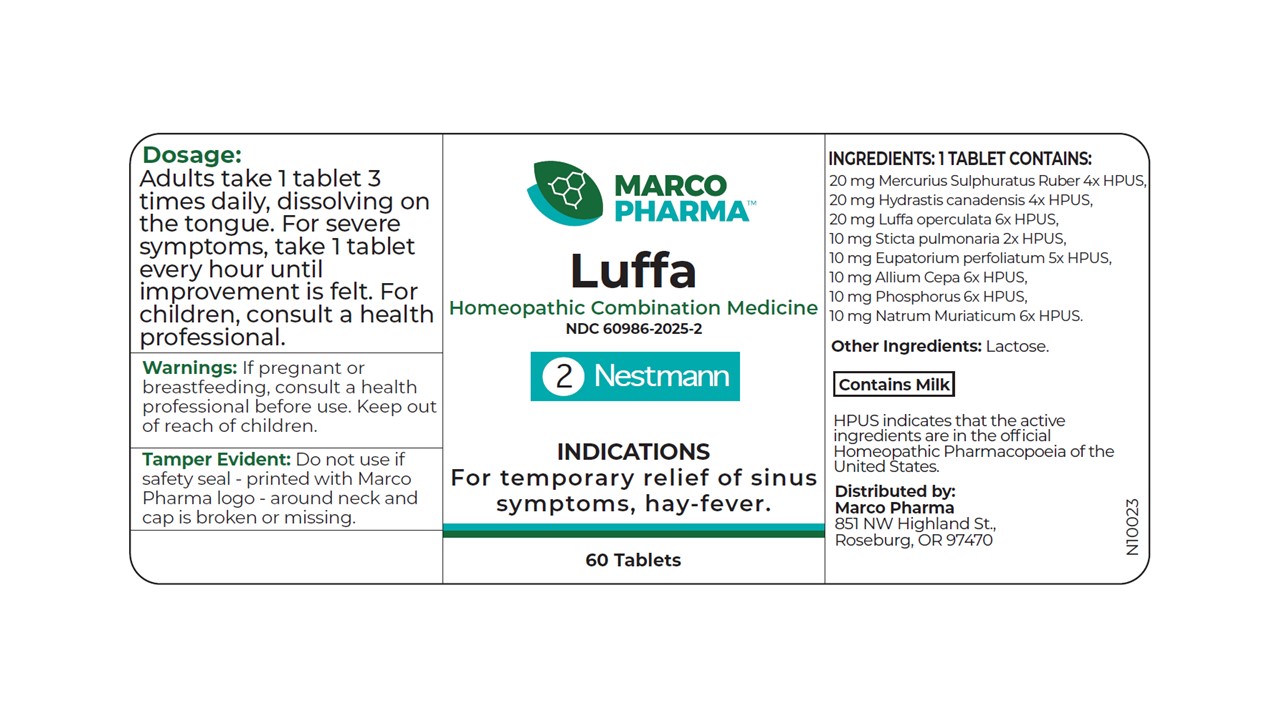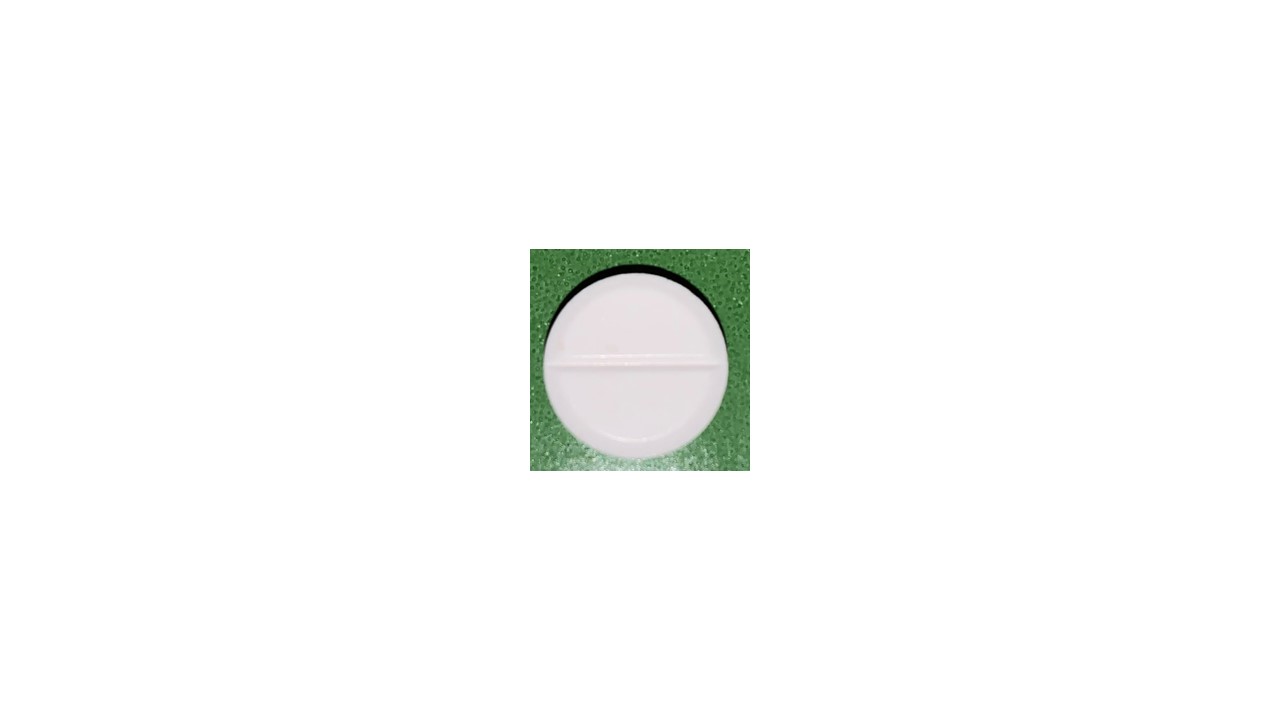 DRUG LABEL: Luffa
NDC: 60986-2025 | Form: TABLET, ORALLY DISINTEGRATING
Manufacturer: Marco Pharma International LLC.
Category: homeopathic | Type: HUMAN OTC DRUG LABEL
Date: 20260112

ACTIVE INGREDIENTS: LUFFA ACUTANGULA FRUIT 6 [hp_X]/1 1; GOLDENSEAL 4 [hp_X]/1 1; MERCURIC SULFIDE 4 [hp_X]/1 1; ONION 6 [hp_X]/1 1; SODIUM CHLORIDE 6 [hp_X]/1 1; PHOSPHORUS 6 [hp_X]/1 1; EUPATORIUM PERFOLIATUM FLOWERING TOP 5 [hp_X]/1 1; LOBARIA PULMONARIA 2 [hp_X]/1 1
INACTIVE INGREDIENTS: LACTOSE

Drug Facts

Active Ingredients

Purging Luffa 6xHPUS

Goldenseal 4xHPUS

Cinnabaris 4xHPUS

Onion 6xHPUS

Salt 6xHPUS

Phosphorus 6xHPUS

Boneset 5xHPUS

Lungwort 2xHPUS

The letters HPUS indicates that the components in this product are officially monographed in the Homeopathic Pharmacopoeia of United Sates.

Purpose

For relief of sinus symptoms; hay-fever.

Keep out of reach of children.

Dosage

Adults take 1 tablet three times daily, dissolving on the tongue. For severe symptoms, take 1 tablet every hour until improvement is felt. Children receive 1/2 or less the adult amount.

Warnings

If pregnant or breast-feeding, consult a health professional before use.

DOSAGE AND ADMINISTRATION

(Read Suggested Use Section)

Inactive Ingredients

In a Lactose base